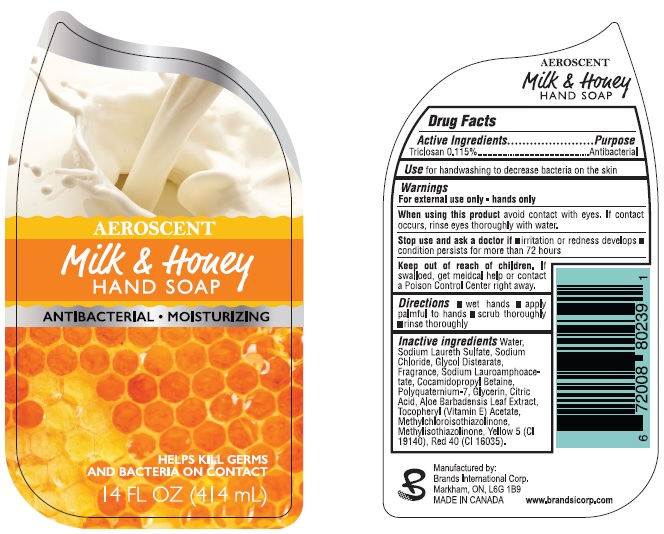 DRUG LABEL: AEROSCENT Milk and Honey Antibacterial Moisturizing
NDC: 50157-108 | Form: SOLUTION
Manufacturer: Brands International
Category: otc | Type: HUMAN OTC DRUG LABEL
Date: 20150623

ACTIVE INGREDIENTS: TRICLOSAN 1.15 mg/1 mL
INACTIVE INGREDIENTS: WATER; SODIUM LAURETH SULFATE; SODIUM CHLORIDE; GLYCOL DISTEARATE; SODIUM LAUROAMPHOACETATE; COCAMIDOPROPYL BETAINE; POLYQUATERNIUM-7 (70/30 ACRYLAMIDE/DADMAC; 1600000 MW); GLYCERIN; CITRIC ACID MONOHYDRATE; ALOE VERA LEAF; .ALPHA.-TOCOPHEROL ACETATE; METHYLCHLOROISOTHIAZOLINONE; FD&C YELLOW NO. 5; FD&C RED NO. 40

Milk & Honey Hand Soap

Drug Facts

Active Ingredients

Triclosan 0.115%

Purpose

Antibacterial

Uses

for handwashing to decrease bacteria on the skin

Warnings

For external use only - hands only

When using this product avoid contact with eyes. If contact occurs, rinse eye thoroughly with water.

Stop use and ask a doctor if

- irritation or redness develops
- condition persists for more than 72 hours

Keep out of reach of children. If swallowed, get medical help or contact a Poison Control Center right away.

Directions

- wet hands
- apply palmful to hands
- scrub thoroughly
- rinse

Inactive ingredients

Water, Sodium Laureth Sulfate, Sodium Chloride, Glycol Distearate, Fragrance, Sodium Laurophoacetate, Cocamidopropyl Betaine, Polyquaternium-7, Glycerin, Citric Acid, Aloe Barbadensis Leaf Extract, Tocopheryl (Vitamin E) Acetate, Methylchloroisothiazolinone, Methylisothiazolinone, Yellow 5 (CI19140), Red 40 (CI16035)

Package Label

AEROSCENT

Milk & Honey HAND SOAP

Antibacterial

Moisturizing

HELPS KILL GERMS AND BACTERIA ON CONTACT

14 FL OZ (414 mL)